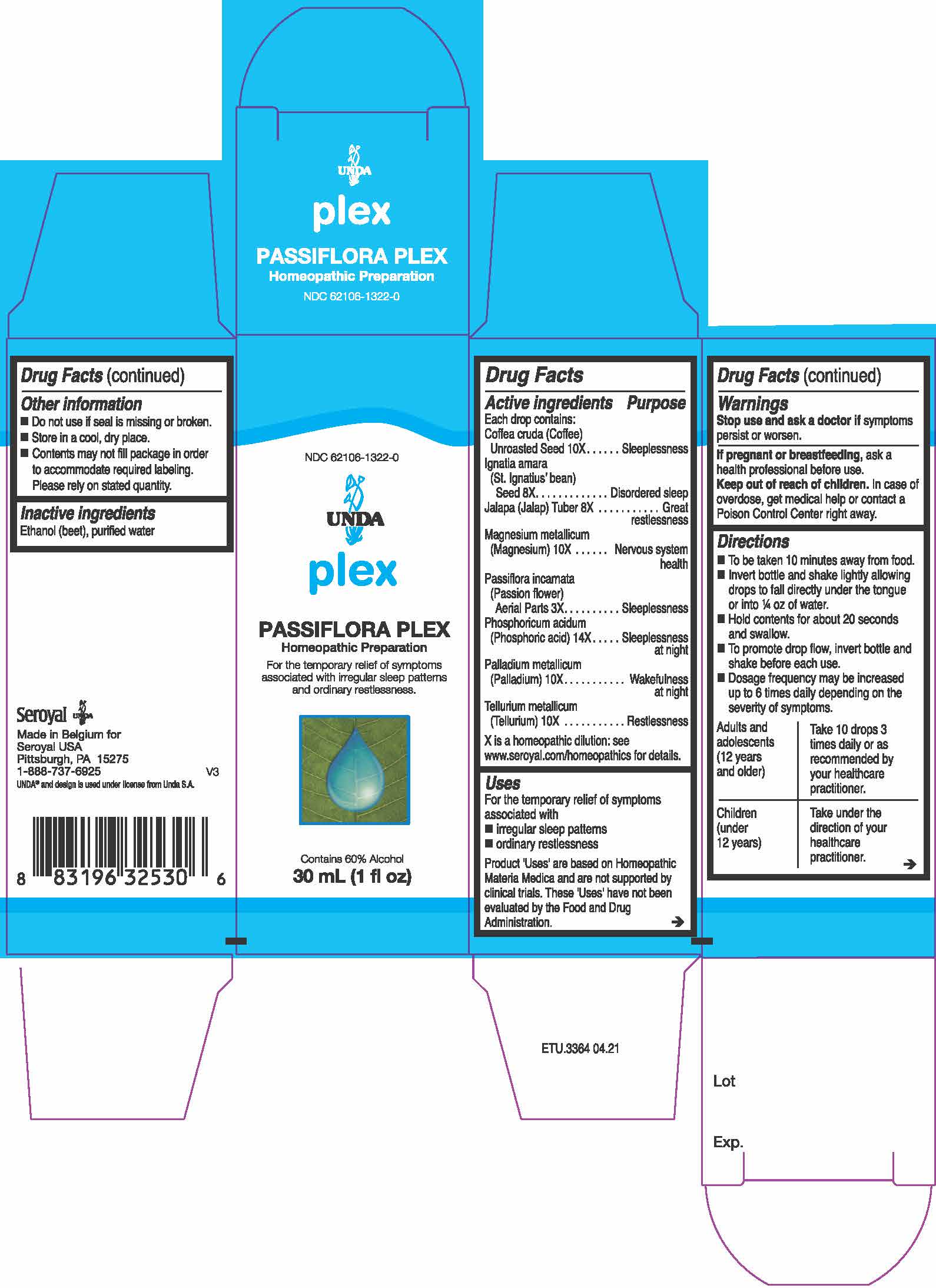 DRUG LABEL: PASSIFLORA PLEX
NDC: 52503-1322 | Form: LIQUID
Manufacturer: San’Up
Category: otc | Type: HUMAN OTC DRUG LABEL
Date: 20211110

ACTIVE INGREDIENTS: PASSIFLORA INCARNATA FLOWERING TOP 3 [hp_X]/30 mL; ARABICA COFFEE BEAN 10 [hp_X]/30 mL; MAGNESIUM 10 [hp_X]/30 mL; STRYCHNOS IGNATII SEED 8 [hp_X]/30 mL; IPOMOEA PURGA ROOT 8 [hp_X]/30 mL; PALLADIUM 10 [hp_X]/30 mL; TELLURIUM 10 [hp_X]/30 mL; PHOSPHORIC ACID 14 [hp_X]/30 mL
INACTIVE INGREDIENTS: WATER 12.07 g/30 mL; ALCOHOL 14.94 g/30 mL

PASSIFLORA PLEX

Active ingredients

Each drop contains:

Coffea cruda (Coffee) Unroasted Seed 10X

Ignatia amara (St. Ignatius’ bean) Seed 8X

Jalapa (Jalap) Tuber 8X

Magnesium metallicum (Magnesium) 10X

Passiflora incarnata (Passion flower) Aerial Parts 3X

Phosphoricum acidum (Phosphoric acid) 14X

Palladium metallicum (Palladium) 10X

Tellurium metallicum (Tellurium) 10X

Keep out of reach of children. In case of overdose, get medical help or contact a Poison Control Center right away.

Uses

For the temporary relief of symptoms associated with irregular sleep patterns and ordinary restlessness.

Uses

For the temporary relief of symptoms associated with irregular sleep patterns and ordinary restlessness.

Product ‘Uses’ are based on Homeopathic Materia Medica and are not supported by clinical trials. These 'Uses' have not been evaluated by the Food and Drug Administration.

Directions

To be taken 10 minutes away from food.

Invert bottle and shake lightly allowing drops to fall directly under the tongue or into ¼ oz of water.

Hold contents for about 20 seconds and swallow.

To promote drop flow, invert bottle and shake before each use.

Dosage frequency may be increased up to 6 times daily depending on the severity of symptoms.

Adults and adolescents (12 years and older) Take 10 drops 3 times daily or as recommended by your healthcare practitioner.

Children (under 12 years) .Take under the direction of your healthcare practitioner.

Directions

To be taken 10 minutes away from food.

Invert bottle and shake lightly allowing drops to fall directly under the tongue or into ¼ oz of water.

Hold contents for about 20 seconds and swallow.

To promote drop flow, invert bottle and shake before each use.

Dosage frequency may be increased up to 6 times daily depending on the severity of symptoms.

Adults and adolescents (12 years and older) Take 10 drops 3 times daily or as recommended by your healthcare practitioner.

Children (under 12 years) .Take under the direction of your healthcare practitioner.

Warnings

Stop use and ask a doctor if symptoms persist or worsen.

If pregnant or breastfeeding, ask a health professional before use.

Keep out of reach of children. In case of overdose, get medical help or contact a Poison Control Center right away.

Inactive ingredients

Ethanol (beet), purified water

PREGNANCY OR BREAST FEEDING

If pregnant or breastfeeding, ask a health professional before use.

Stop use and ask a doctor if symptoms persist or worsen.

OVERDOSAGE

In case of overdose, get medical help or contact a Poison Control Center right away.

Do not use if seal is missing or broken.

Store in a cool, dry place.

Contents may not fill package in order to accommodate required labeling. Please rely on stated quantity.

Indications & Usage section

Addition of:

"Product ‘Uses’ are based on Homeopathic Materia Medica and are not supported by clinical trials. These 'Uses' have not been evaluated by the Food and Drug Administration."

PACKAGE LABEL

NDC 62106-1322-0

UNDA

PLEX

PASSIFLORA PLEX

Homeopathic Preparation

For the temporary relief of symptoms associated with irregular sleep patterns and ordinary restlessness.

Contains 60% Alcohol

30 mL (1 fl oz)